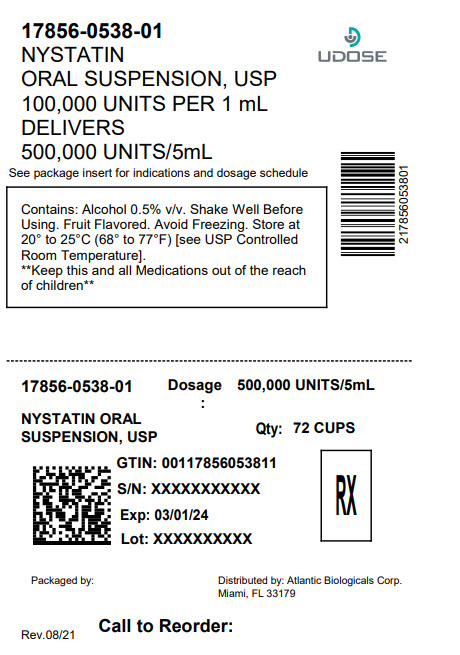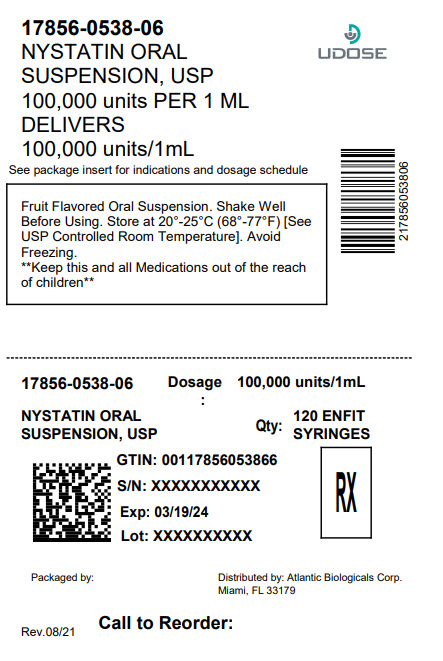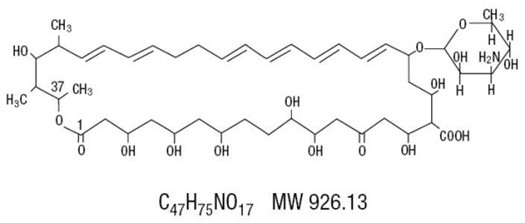 DRUG LABEL: Nystatin
NDC: 17856-0538 | Form: SUSPENSION
Manufacturer: ATLANTIC BIOLOGICALS CORP.
Category: prescription | Type: HUMAN PRESCRIPTION DRUG LABEL
Date: 20250731

ACTIVE INGREDIENTS: NYSTATIN 100000 [USP'U]/1 mL
INACTIVE INGREDIENTS: WATER; MAGNESIUM ALUMINUM SILICATE; PROPYLENE GLYCOL; GLYCERIN; SUCROSE; POTASSIUM PHOSPHATE, DIBASIC; ALCOHOL; METHYLPARABEN; PROPYLPARABEN; D&C YELLOW NO. 10; FD&C RED NO. 40

NYSTATIN ORAL
SUSPENSION, USP

(100,000 units per mL)

Rx only

DESCRIPTION

Nystatin is an antimycotic polyene antibiotic obtained from Streptomyces noursei. Structural formula:

Nystatin Oral Suspension, for oral administration, contains 100,000 USP Nystatin Units per mL. Inactive ingredients: alcohol (≤ 1% v/v), artificial wild cherry flavor, banana flavor, D&C yellow #10, FD&C red #40, glycerin, USP, magnesium aluminum silicate, methylparaben, NF, potassium phosphate dibasic, USP, propylene glycol, USP, propylparaben, NF, purified water, USP and sucrose 33.5%. May also contain citric acid, USP for pH adjustment.

CLINICAL PHARMACOLOGY

Pharmacokinetics

Gastrointestinal absorption of nystatin is insignificant. Most orally administered nystatin is passed unchanged in the stool. In patients with renal insufficiency receiving oral therapy with conventional dosage forms, significant plasma concentrations of nystatin may occasionally occur.

Microbiology

Nystatin is both fungistatic and fungicidal in vitroagainst a wide variety of yeasts and yeast-like fungi. Candida albicansdemonstrates no significant resistance to nystatin in vitroon repeated subculture in increasing levels of nystatin; other Candidaspecies become quite resistant. Generally, resistance does not develop in vivo. Nystatin acts by binding to sterols in the cell membrane of susceptible Candidaspecies with a resultant change in membrane permeability allowing leakage of intracellular components. Nystatin exhibits no appreciable activity against bacteria, protozoa, or viruses.

INDICATIONS AND USAGE

Nystatin Oral Suspension is indicated for the treatment of candidiasis in the oral cavity.

CONTRAINDICATIONS

The preparation is contraindicated in patients with a history of hypersensitivity to any of its components.

PRECAUTIONS

General

This medication is not to be used for the treatment of systemic mycoses. Discontinue treatment if sensitization or irritation is reported during use.

Carcinogenesis, Mutagenesis, Impairment of Fertility

No long-term animal studies have been performed to evaluate carcinogenic potential. There also have been no studies to determine mutagenicity or whether this medication affects fertility in males or females.

Pregnancy

Teratogenic Effects Category C

Animal reproduction studies have not been conducted with nystatin oral suspension. It is also not known whether nystatin oral suspension can cause fetal harm when administered to a pregnant woman or can affect reproduction capacity. Nystatin oral suspension should be given to a pregnant woman only if clearly needed.

Nursing Mothers

It is not known whether nystatin is excreted in human milk. Because many drugs are excreted in human milk, caution should be exercised when nystatin is administered to a nursing woman.

Pediatric Use

See DOSAGE AND ADMINISTRATION.

ADVERSE REACTIONS

Nystatin is well tolerated even with prolonged therapy. Oral irritation and sensitization have been reported. (See PRECAUTIONS: General).

Gastrointestinal:Diarrhea (including one case of bloody diarrhea), nausea, vomiting, gastrointestinal upset/disturbances.

Dermatologic:Rash, including urticaria has been reported rarely. Stevens-Johnson syndrome has been reported very rarely.

Other:Tachycardia, bronchospasm, facial swelling, and non-specific myalgia have also been rarely reported.

OVERDOSAGE

Oral doses of nystatin in excess of five million units daily have caused nausea and gastrointestinal upset. There have been no reports of serious toxic effects of superinfections (see CLINICAL PHARMACOLOGY, Pharmacokinetics).

DOSAGE AND ADMINISTRATION

INFANTS: 2 mL (200,000 units) four times daily (in infants and young children, use dropper to place one-half of dose in each side of mouth and avoid feeding for 5 to 10 minutes).
NOTE: Limited clinical studies in premature and low birth weight infants indicate that 1 mL four times daily is effective.

CHILDREN AND ADULTS: 4–6 mL (400,000 to 600,000 units) four times daily (one-half of dose in each side of mouth). The preparation should be retained in the mouth as long as possible before swallowing.

Continue treatment for at least 48 hours after perioral symptoms have disappeared and cultures demonstrate eradication of Candida albicans.

HOW SUPPLIED

Nystatin Oral Suspension, USP, 100,000 USP Nystatin Units per mL, is available as a fruit flavored, light creamy yellow, ready-to-use suspension.

60 mL bottles with a calibrated dropper and 1 Pint (473 mL) bottles.

Storage

Store at 20° to 25°C (68° to 77°F) [see USP Controlled Room Temperature]. Avoid freezing

Rx Only

Product No.: 8537

Manufactured For:
Wockhardt USA, LLC
Parsippany, NJ 07054

Manufactured By:
Morton Grove Pharmaceuticals, Inc.
Morton Grove, IL 60053

28537B
REV. 09-09

Distributed by Atlantic Biologicals

Miami, Fl 33179

PRINCIPAL DISPLAY PANEL - 60 mL Bottle Carton

NYSTATIN ORAL

SUSPENSION, USP
(100,000 units
per mL)

Fruit Flavored

Rx Only